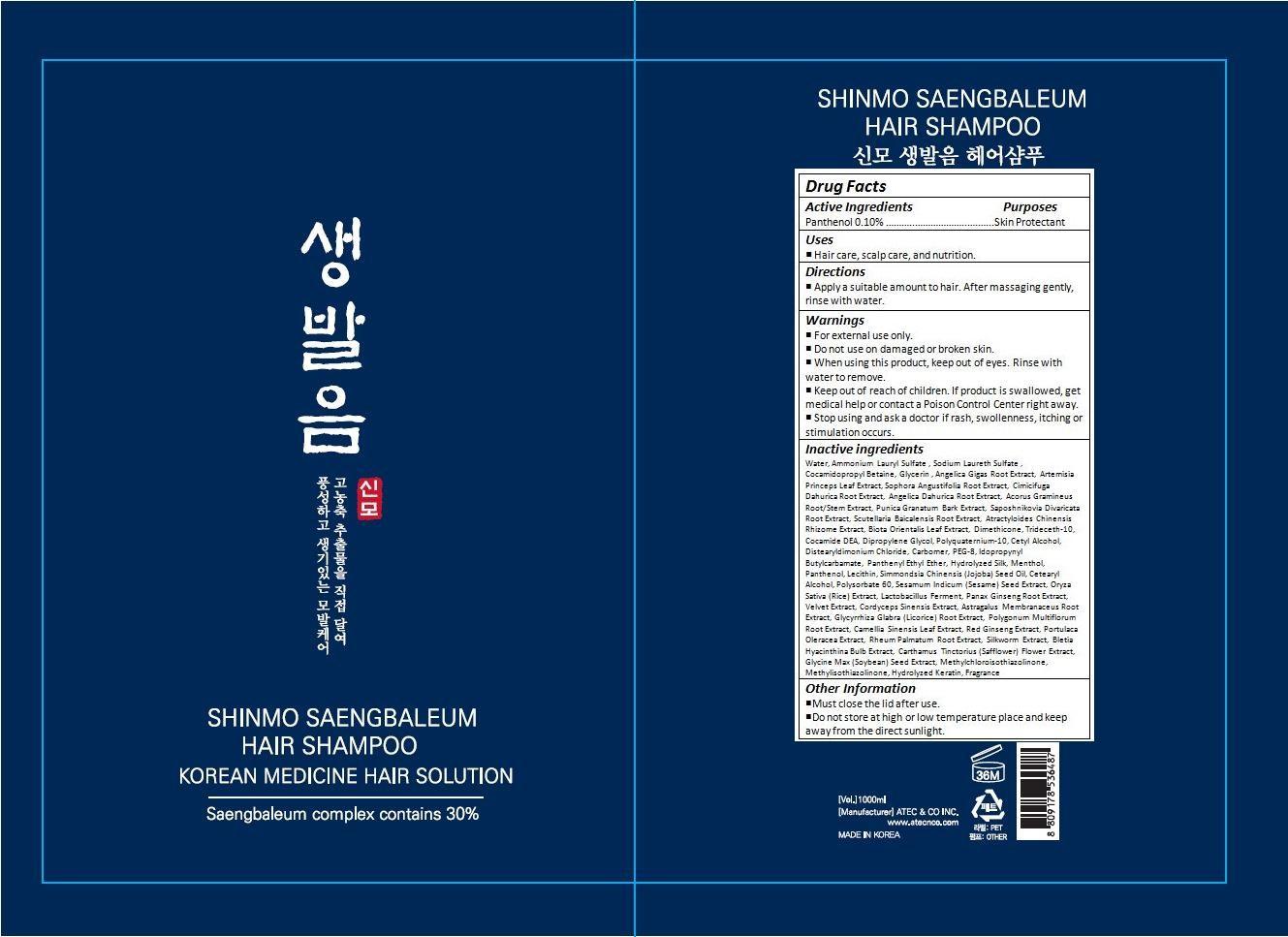 DRUG LABEL: SHINMO SAENGBALEUM HAIR
NDC: 69978-001 | Form: SHAMPOO
Manufacturer: ATEC&CO INC.
Category: otc | Type: HUMAN OTC DRUG LABEL
Date: 20150716

ACTIVE INGREDIENTS: PANTHENOL 0.95 g/958.50 g
INACTIVE INGREDIENTS: WATER; AMMONIUM LAURYL SULFATE; SODIUM LAURETH-3 SULFATE; COCAMIDOPROPYL BETAINE; GLYCERIN; ANGELICA GIGAS ROOT; ARTEMISIA PRINCEPS LEAF; SOPHORA FLAVESCENS ROOT; ACTAEA DAHURICA ROOT; ANGELICA DAHURICA ROOT; ACORUS GRAMINEUS ROOT; PUNICA GRANATUM ROOT BARK; SAPOSHNIKOVIA DIVARICATA ROOT; SCUTELLARIA BAICALENSIS ROOT; ATRACTYLODES LANCEA ROOT; PLATYCLADUS ORIENTALIS LEAF; DIMETHICONE; TRIDECETH-10; COCO DIETHANOLAMIDE; DIPROPYLENE GLYCOL; POLYQUATERNIUM-10 (125 MPA.S AT 2%); CETYL ALCOHOL; DISTEARYLDIMONIUM CHLORIDE; CARBOMER HOMOPOLYMER TYPE C (ALLYL PENTAERYTHRITOL CROSSLINKED); POLYETHYLENE GLYCOL 400; IODOPROPYNYL BUTYLCARBAMATE; PANTHENYL ETHYL ETHER ACETATE; BOMBYX MORI FIBER; MENTHOL, UNSPECIFIED FORM; EGG PHOSPHOLIPIDS; JOJOBA OIL; CETOSTEARYL ALCOHOL; POLYSORBATE 60; SESAME SEED; RICE GERM; ASIAN GINSENG; OPHIOCORDYCEPS SINENSIS; ASTRAGALUS PROPINQUUS ROOT; GLYCYRRHIZA GLABRA; FALLOPIA MULTIFLORA ROOT; GREEN TEA LEAF; PURSLANE; RHEUM PALMATUM ROOT; BLETILLA STRIATA BULB; SAFFLOWER; SOYBEAN; METHYLCHLOROISOTHIAZOLINONE; METHYLISOTHIAZOLINONE

Drug Facts

ACTIVE INGREDIENT

PANTHENOL 0.10%

PURPOSE

Cleansing

INDICATIONS AND USAGE

Strengthen hair roots and scalp. Keeps the hair rich and
Healthy.

DOSAGE AND ADMINISTRATION

Apply a suitable amount to hair. After massaging gently, rinse with water.

WARNINGS

For external use only.

Do not use on damaged or broken skin.

When using this product, keep out of eyes. Rinse with water to remove.

Stop using and ask a doctor if rash, swollenness, itching or stimulation occurs.

KEEP OUT OF REACH OF CHILDREN

Keep out of reach of the children. If product is swallowed, get medical help or contact a poison control center right away.

INACTIVE INGREDIENT

Water, Ammonium Lauryl Sulfate , Sodium Laureth Sulfate , Cocamidopropyl Betaine, Glycerin , Angelica Gigas Root Extract, Artemisia Princeps Leaf Extract, Sophora Angustifolia Root Extract, Cimicifuga Dahurica Root Extract, Angelica Dahurica Root Extract, Acorus Gramineus Root/Stem Extract, Punica Granatum Bark Extract, Saposhnikovia Divaricata Root Extract, Scutellaria Baicalensis Root Extract, Atractyloides Chinensis Rhizome Extract, Biota Orientalis Leaf Extract, Dimethicone, Trideceth-10, Cocamide DEA, Dipropylene Glycol, Polyquaternium-10, Cetyl Alcohol, Distearyldimonium Chloride, Carbomer, PEG-8, Idopropynyl Butylcarbamate, Panthenyl Ethyl Ether, Hydrolyzed Silk, Menthol, Panthenol, Lecithin, Simmondsia Chinensis (Jojoba) Seed Oil, Cetearyl Alcohol, Polysorbate 60, Sesamum Indicum (Sesame) Seed Extract, Oryza Sativa (Rice) Extract, Lactobacillus Ferment, Panax Ginseng Root Extract, Velvet Extract, Cordyceps Sinensis Extract, Astragalus Membranaceus Root Extract, Glycyrrhiza Glabra (Licorice) Root Extract, Polygonum Multiflorum Root Extract, Camellia Sinensis Leaf Extract, Red Ginseng Extract, Portulaca Oleracea Extract, Rheum Palmatum Root Extract, Silkworm Extract, Bletia Hyacinthina Bulb Extract, Carthamus Tinctorius (Safflower) Flower Extract, Glycine Max (Soybean) Seed Extract, Methylchloroisothiazolinone, Methylisothiazolinone, Hydrolyzed Keratin, Fragrance